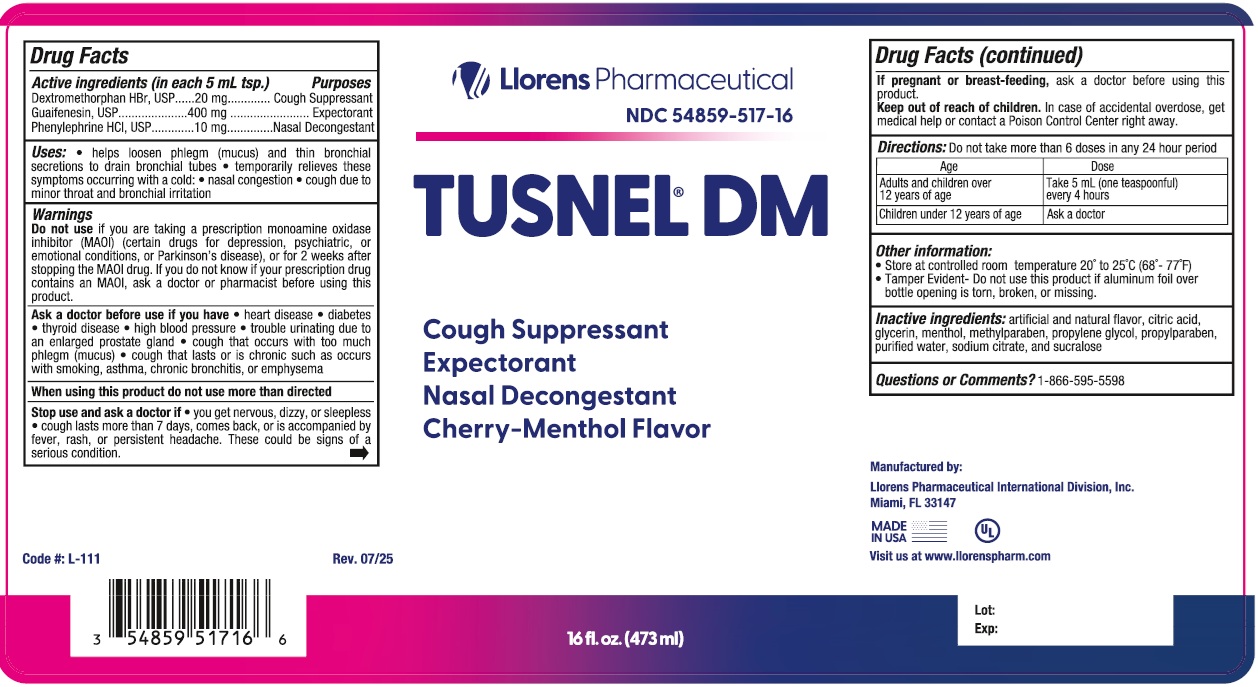 DRUG LABEL: Tusnel
NDC: 54859-517 | Form: LIQUID
Manufacturer: Llorens Pharmaceutical International Division, Inc.
Category: otc | Type: HUMAN OTC DRUG LABEL
Date: 20251229

ACTIVE INGREDIENTS: DEXTROMETHORPHAN HYDROBROMIDE 20 mg/5 mL; GUAIFENESIN 400 mg/5 mL; PHENYLEPHRINE HYDROCHLORIDE 10 mg/5 mL
INACTIVE INGREDIENTS: ANHYDROUS CITRIC ACID; GLYCERIN; MENTHOL; METHYLPARABEN; PROPYLENE GLYCOL; PROPYLPARABEN; WATER; SODIUM CITRATE; SUCRALOSE

Llorens-TusnelDM 517

ACTIVE INGREDIENT

In each 5 mL

Dextromethorphan HBr - 20 mg

Guaifenesin - 400 mg

Phenylephrine HCl - 10 mg

Purpose

Cough Suppressant

Expectorant

Nasal Decongestant

Uses

- helps loosen phlegm (mucus) and thin bronchial secretions to drain bronchial tubes
- temporarily relieves these symptoms occurring with a cold
- nasal congestion •cough due to minor throat and bronchial irritation

Warnings

Do not use if you are taking a monoamine oxidase inhibitor (MAOI) (certain drugs for depression, psychiatric, or emotional conditions, or Parkinson's disease), or for 2 weeks after stopping the MAOI drug. If you do not know if your prescription drug contains an MAOI, ask a doctor or pharmacist before using this product.

Ask a doctor before use if you have

- heart disease
- high blood pressure
- thyroid disease
- diabetes
- difficulty in urination due to enlargment of prostate gland
- a cough with too much phlegm (mucus)
- a persistent or chronic cough as occurs with smoking, asthma, chronic bronchitis, or emphysema

Stop use and ask a doctor if you get

- nervousness, dizziness, or sleeplessness occur
- cough lasts for more than 7 days, comes back or occurs with a fever, rash or headache that lasts. These could be signs of a serious condition.

PREGNANCY OR BREAST FEEDING

If pregnant or breast-feeding, ask a doctor before using this product

Keep out of reach of children.In case of accidental overdose, seek advice of a doctor or contact a Poison Control Center right away.

DOSAGE AND ADMINISTRATION

Directions: Do not exceed 6 doses in 24 hour

Age | Dose
Adults and children over 12 years of age | Take 5 mL (one teaspoonful) every 4 hours
Children under 12 years of age | Ask a doctor

INACTIVE INGREDIENT

Inactive ingredients:artificial and natural flavor, citric acid, glycerin, menthol, methylparaben, propylene glycol, propylparaben, purified water, sodium citrate, and sucralose

Questions or Comments?1-866-595-5598